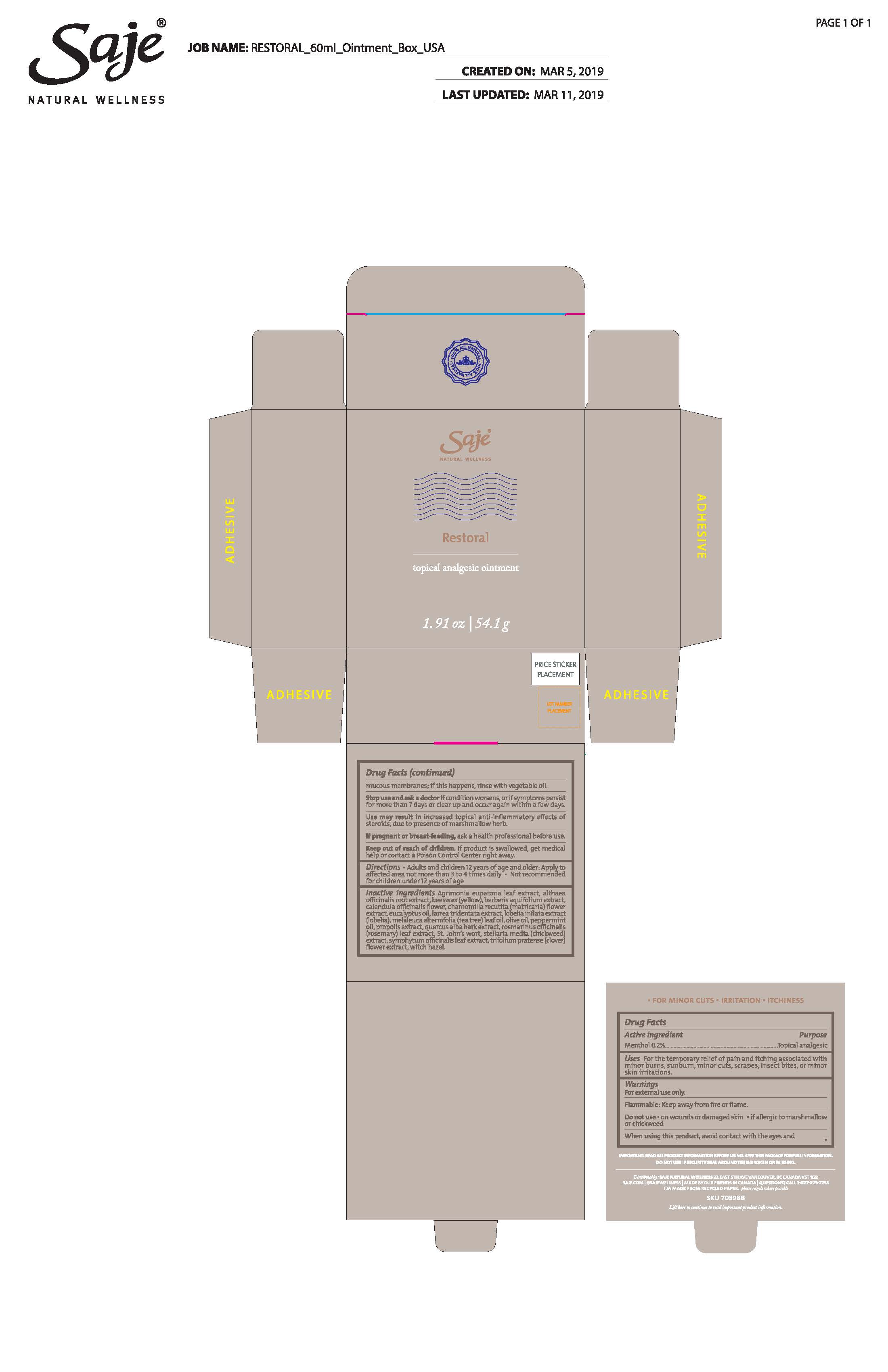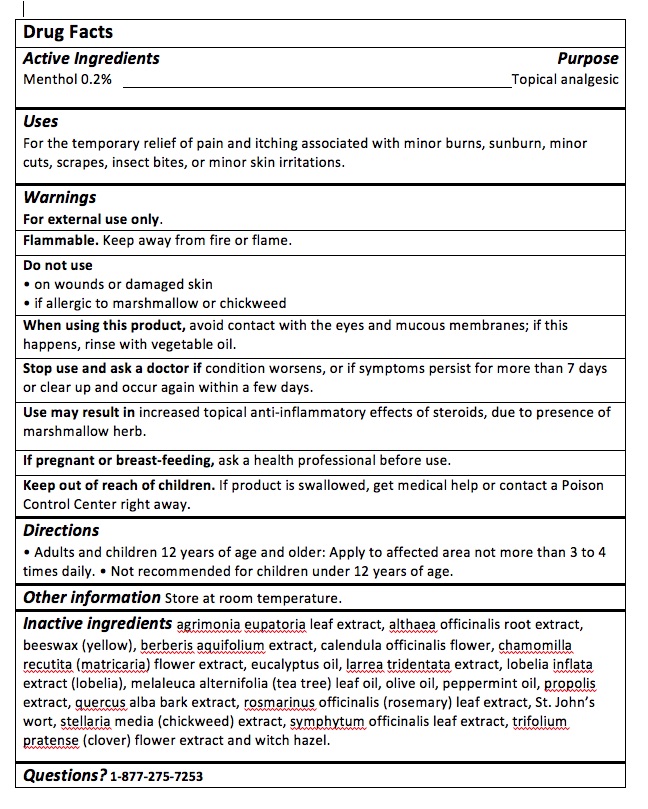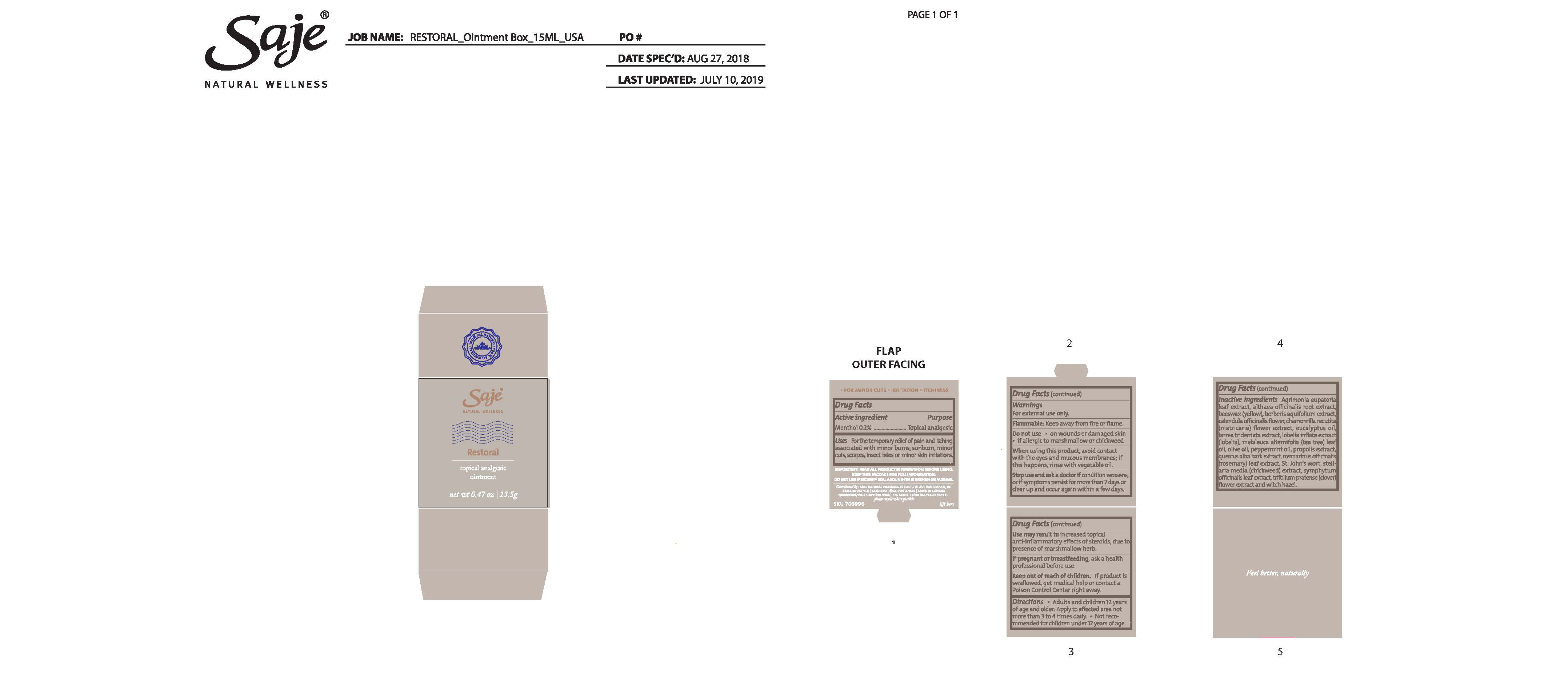 DRUG LABEL: Restoral
NDC: 70983-022 | Form: OINTMENT
Manufacturer: Saje Natural Business Inc.
Category: otc | Type: HUMAN OTC DRUG LABEL
Date: 20260113

ACTIVE INGREDIENTS: MENTHOL 0.2 g/100 g
INACTIVE INGREDIENTS: MATRICARIA CHAMOMILLA FLOWERING TOP; LOBELIA INFLATA LEAF; OLIVE OIL; COMFREY ROOT; PEPPERMINT OIL; ST. JOHN'S WORT; STELLARIA MEDIA; TRIFOLIUM PRATENSE FLOWER; ALTHAEA OFFICINALIS ROOT; YELLOW WAX; BERBERIS AQUIFOLIUM ROOT; CALENDULA OFFICINALIS FLOWER; EUCALYPTUS OIL; LARREA TRIDENTATA LEAF; TEA TREE OIL; PROPOLIS WAX; QUERCUS ALBA BARK; ROSEMARY; WITCH HAZEL; AGRIMONIA EUPATORIA LEAF

Restoral

Active Ingredient

Menthol 0.2%

Purpose

Topical analgesic

Uses

For the temporary relief of pain and itching associated with minor burns, sunburn, minor cuts, scrapes, insect bites, or minor skin irritations

Warnings

For external use only

Flammable - keep away from fire or flame

Use may result in increased topical anti-inflammatory effects of steroids, due to presence of marshmallow herb

When using this product

Avoid contact with eyes and mucous membranes; if this happens, rinse with vegetable oil

Stop use and ask a doctor

if condition worsens, or if symptoms persist for more than 7 days or clear up and occur again within a few days

Do not use

On wounds or damaged skin

If allergic to marshmallow root or chickweed

if pregnant or breast-feeding

ask a health professional before use

keep out of reach of children

if product is swallowed, get medical help or contact a Poison Control Centre right away

Directions

Adults and children 12 years of age and older: Apply to affected area not more than 3 to 4 times daily.

Not recommended for children under 12 years of age.

Inactive ingredients

Agrimonia eupatoria leaf extract, althaea officinalis root extract, beeswax (yellow), berberis aquifolium extract, calendula officinalis flower, chamomilla recutita (matricaria) flower extract, eucalyptus oil, larrea tridentata extract, lobelia inflata extract (lobelia), melaleuca alternifolia (tea tree) leaf oil, olive oil, peppermint oil, propolis extract, quercus alba bark extract, rosmarinus officinalis (rosemary) leaf extract, St. John’s wort, stellaria media (chickweed) extract, symphytum officinalis leaf extract, trifolium pratense (clover) flower extract and witch hazel

Questions?

1-877-275-7253

Principle Display Panel information

Restoral

topical analgesic ointment

net wt. 54.1g (1.91oz) and net wt. 13.5g (0.47oz)